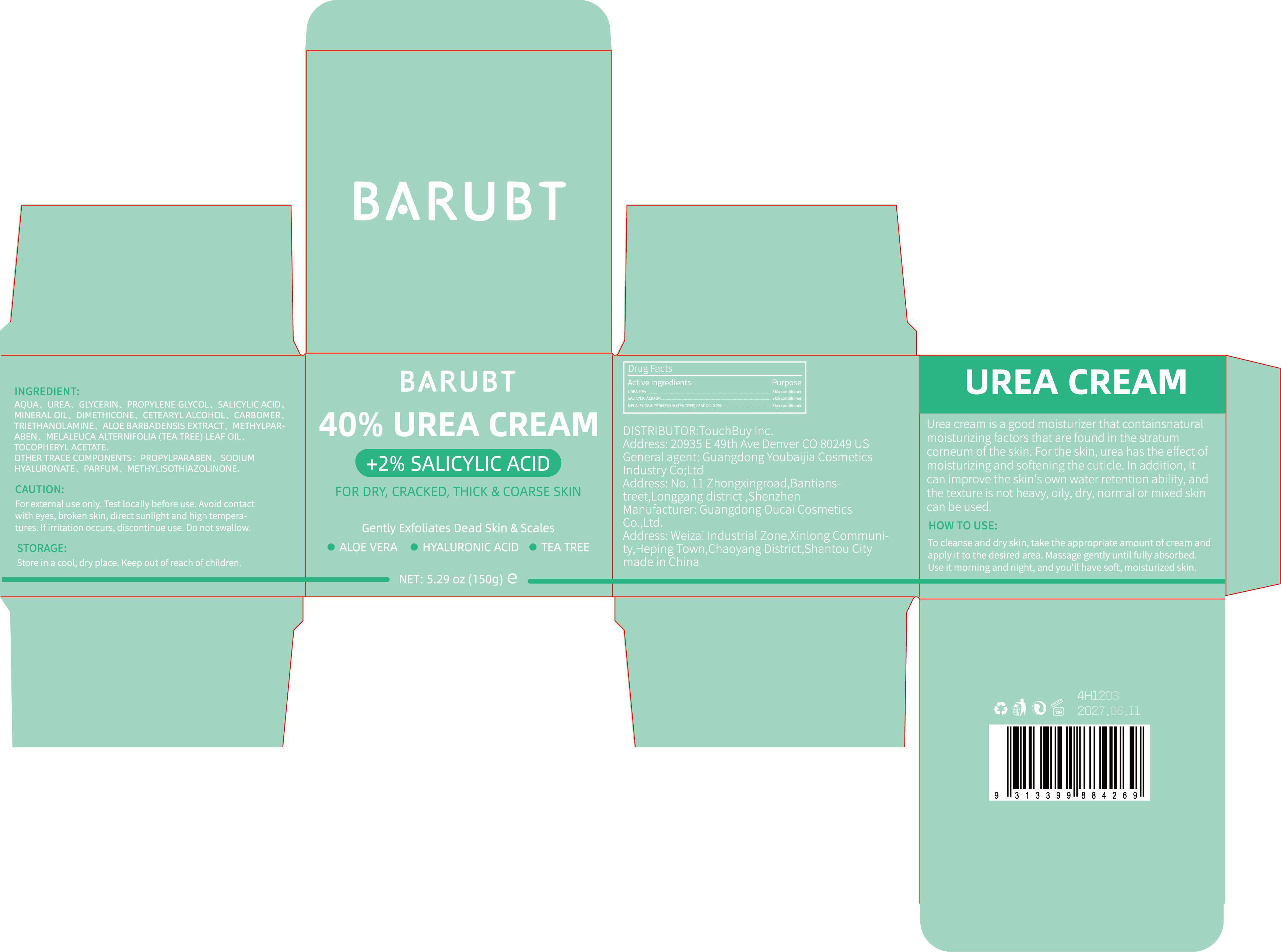 DRUG LABEL: BARUBT Urea Cream
NDC: 84712-023 | Form: CREAM
Manufacturer: Guangdong Youbaijia Cosmetic Industry Co., Ltd
Category: otc | Type: HUMAN OTC DRUG LABEL
Date: 20240918

ACTIVE INGREDIENTS: MELALEUCA ALTERNIFOLIA (TEA TREE) LEAF OIL 0.3 g/150 g; SALICYLIC ACID 3 g/150 g; UREA 60 g/150 g
INACTIVE INGREDIENTS: GLYCERIN 7.5 g/150 g; PROPYLENE GLYCOL 7.5 g/150 g

ACTIVE INGREDIENT

UREA 40%
SALICYLIC ACID 2%

MELALEUCAALTERNIFOLIA (TEA TREELLEAFOIL 0.2%

INACTIVE INGREDIENT

AQUA
GLYCERIN
PROPYLENE GLYCOL
MINERAL OIL
DIMETHICONE
CETEARYL ALCOHOL
CARBOMER
TRIETHANOLAMINE
ALOE BARBADENSIS EXTRACT
METHYLPARABEN
TOCOPHERYL ACETATE
PROPYLPARABEN
SODIUM HYALURONATE
PARFUM
METHYLISOTHIAZOLINONE

Do not use on damaged skin.

Keep away from children. Do not swallow.

PURPOSE

moisturizing and softening the cuticle

QUESTIONS

Contact name: Jessie Peng
Company phone number: +1 818 579 7288
Company e-mail: jessie@registeragentllc.com

STOP USE

lf skin becomes red or irritated, discontinue use immediately and wash with water.

WHEN USING

keep out of eyes. Rinse with water to remove.

WARNINGS

For external use only.

STORAGE AND HANDLING

Keep away from light and in a dry place.

INDICATIONS AND USAGE

Urea cream is a good moisturizer that containsnatural moisturizing factors that are found in the stratum corneum of the skin. For the skin, urea has the effect of moisturizing and softening the cuticle.In addition, it can improve the skin's own water retention ability, and the texture is not heavy, oily, dry, normal or mixed skin can be used.

DOSAGE AND ADMINISTRATION

To cleanse and dry skin, take the appropriate amount of cream and apply it to the desired area. Massage gently until fully absorbed. Use it morning and night, and you'll have soft, moisturized skin.